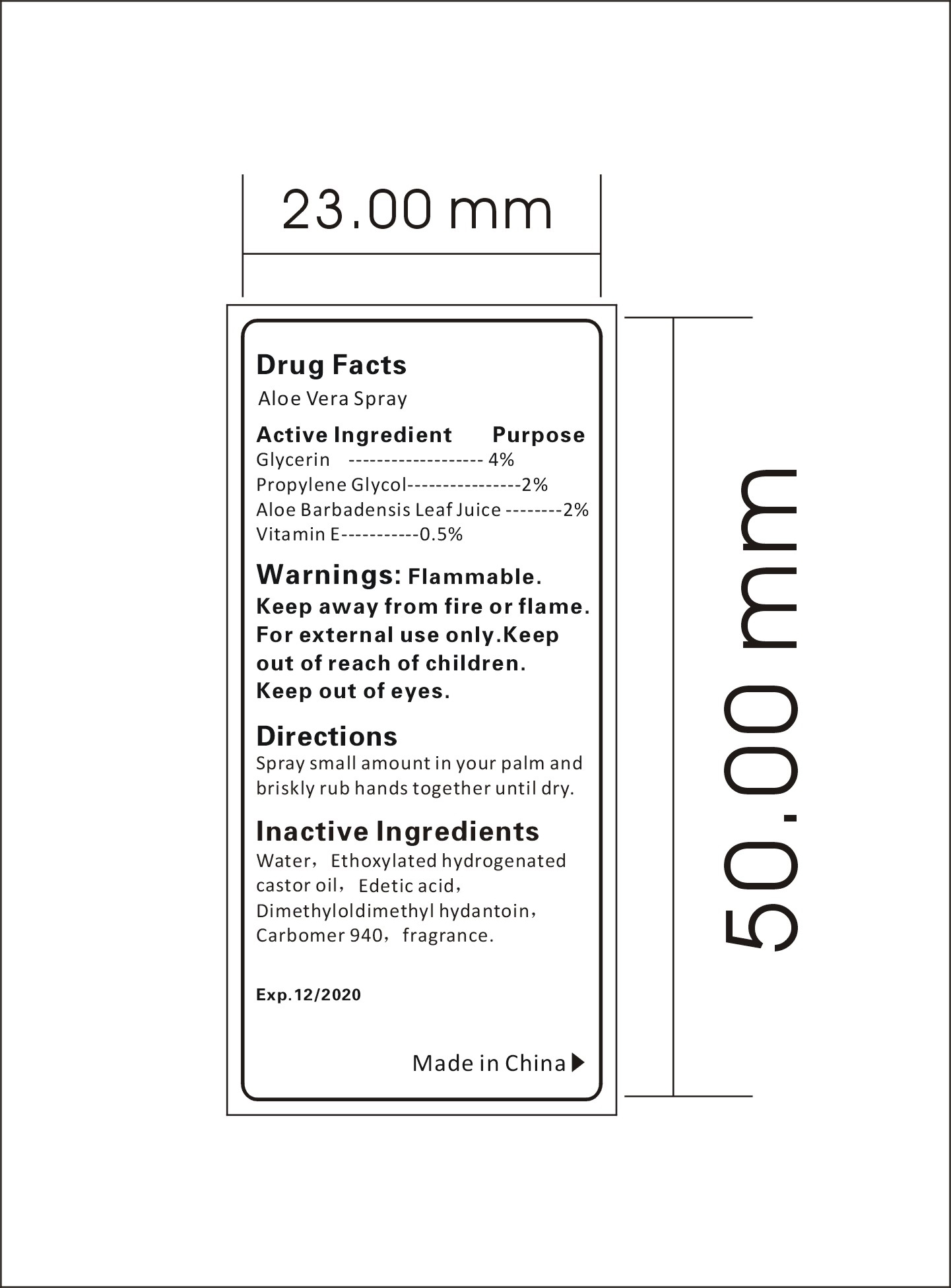 DRUG LABEL: Aloe Vera Sprayer
NDC: 47993-221 | Form: LIQUID
Manufacturer: NINGBO JIANGBEI OCEAN STAR TRADING CO.,LTD
Category: otc | Type: HUMAN OTC DRUG LABEL
Date: 20171206

ACTIVE INGREDIENTS: GLYCERIN 4 g/100 g; PROPYLENE GLYCOL 2 g/100 g; ALOE VERA LEAF 2 g/100 g; TOCOPHEROL 0.5 g/100 g
INACTIVE INGREDIENTS: WATER 85.03 g/100 g; HYDROGENATED CASTOR OIL 6 g/100 g; EDETIC ACID 0.1 g/100 g; AROMADENDRIN 0.3 g/100 g; DMDM HYDANTOIN 0.05 g/100 g; CARBOMER 940 0.02 g/100 g

Active Ingredients

Active ingredients--------------purpose

Glycerine..........4%

Propylene Glycol..........2%

Aloe Barbadensis Leaf Juice.........2%

VitaminE.........0.5%

Uses:
Keep skin moist. Recommended for repeated use.

Warnings:

Keep away from fire or flame.For external use only.Keep out of reach of children.Keep out of reach of eyes.

Directions:

Spray small amount in your palm and briskly rub hands together until dry.

Other Information

Do not store above 110F(43C) May discolor certain fabric or surfaces. Harmful to wood finishes and plastics.

KEEP OUT OF REACH OF CHILDREN

Children under 6 years of age should be super vised when using this product.

Inactive Ingredients:

Water,Ethoxylated hydrogenated castor oil,Edetic acid,Dimethyloldimethy hydantion,Carbomer 940,Fragrance.